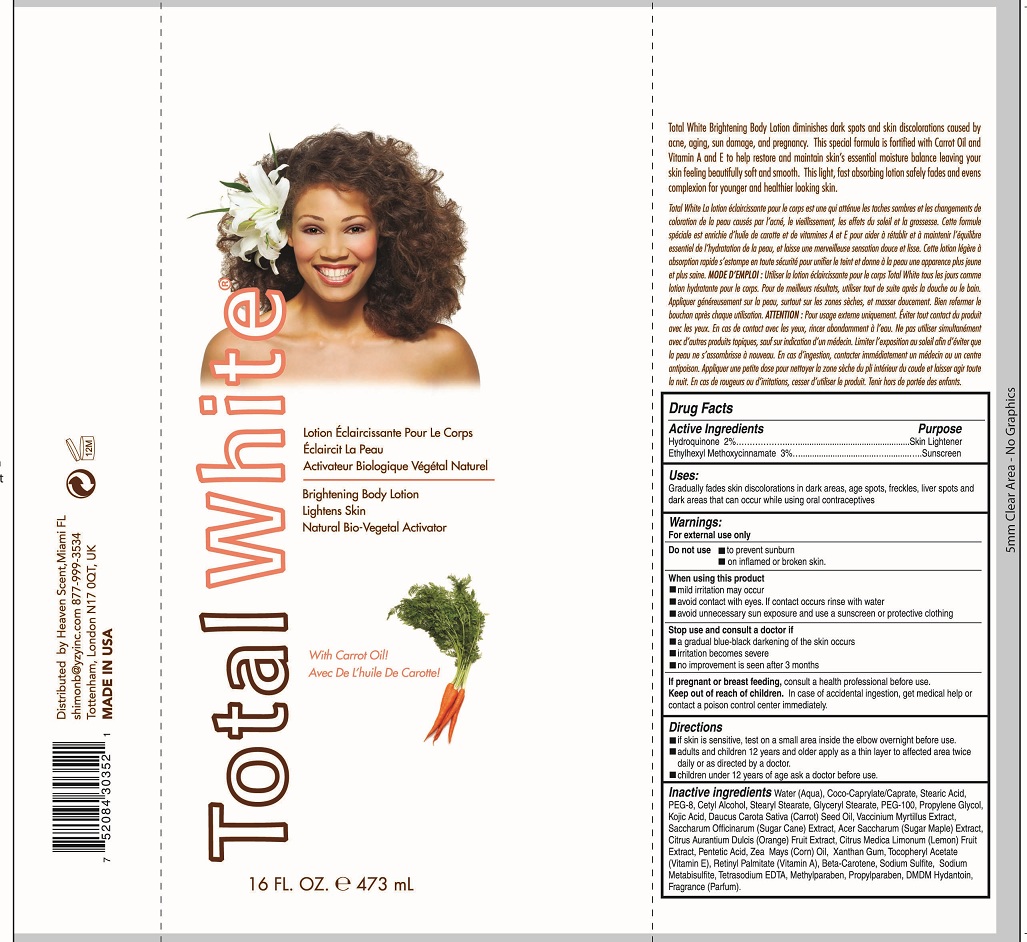 DRUG LABEL: Total White Brightening 
NDC: 53218-001 | Form: LOTION
Manufacturer: YZY Inc
Category: otc | Type: HUMAN OTC DRUG LABEL
Date: 20120607

ACTIVE INGREDIENTS: Octinoxate 14.19 mg/473 mL; Hydroquinone 9.46 mg/473 mL
INACTIVE INGREDIENTS: Water; Coco-caprylate/caprate; Stearic Acid; Polyethylene Glycol 400; Cetyl Alcohol; Stearyl Stearate; Glyceryl Monostearate; Propylene Glycol; Kojic Acid; Carrot Seed Oil; Pentetic Acid; Corn Oil; Xanthan Gum; .alpha.-tocopherol Acetate; Vitamin A Palmitate; .beta.-carotene; Sodium Sulfite; Sodium Metabisulfite; Edetate Sodium; Methylparaben; Propylparaben; Dmdm Hydantoin; Polyethylene Glycol 4500; Sugarcane; Orange; Lemon; Bilberry

Drug Facts

Active Ingredients

Hydroquinone 2%
Ethylhexyl Methoxycinnamate 3%

Purpose

Hydroquinone 2% ............................... Skin Lightener
Ethylhexyl Methoxycinnamate 3% ..... Sunscreen

Uses:

Gradually fades skin discolorations in dark areas, age spots, freckles, liver spots and dark areas that can occur while using oral contraceptives

Warnings:

For external use only

Do Not Use

To prevent sunburn • On inflamed or broken skin

When using this product

• Mild irritation may occur
• Avoid contact with eyes. If contact occurs rinse with water.
• Avoid unnecessary sun exposure and use a sunscreen or protective clothing

Stop use and consult a doctor if

• A gradual blue-black darkening of the skin ocurs
• Irritation becomes severe
• No improvement is seen after 3 months

If pregnant or breast feeding,

consult a health professional before use.

Keep out of reach of children.

In case of accidental ingestion, get medical help or contact a poison control center immediately.

Directions

• If skin is sensitive, test on a small area inside the elbow overnight before use.
• adults and children 12 years and older apply as a thin layer to affected area twice daily or as directed by a doctor.
• Children under 12 years of age ask a doctor before use.

Inactive ingredients

Water (Aqua), Coco-Caprylate/Caprate, Stearic Acid, PEG-8, Cetyl Alcohol, Stearyl Stearate, Glyceryl Stearate, PEG-100, Propylene Glycol, Kojic Acid, Daucus Carota Sative (Carrot) Seed Oil, Vaccinium Myrtillus Extract, Saccharum Officinarum (Sugar Cane) Extract, Acer Saccharum (Sugar Maple) Extract, Citrus Aurantium Dulcis (Orange) Fruit Extract, Citrus Medica Limonum (Lemon) Fruit Extract, Pentetic Acid, Zea Mays (Corn) Oil, Xanthan Gum, Tocopheryl Acetate (Vitamin E), Retinyl Palmitate (Vitamin A), Beta-Carotene, Sodium Sulfite, Sodium Metabisulfite, Tetrasodium EDTA, Methylparaben, Propylparaben, DMDM Hydantoin, Fragrance (Parfum)

PRINCIPAL DISPLAY PANEL

Total White
Brightening Body Lotion
Lightens Skin
Natural Bio-vegetal Activation
With Carrot Oil
16 FL. OZ e 473 mL
Distributed by Heaven Scent, Miami FL
shimonb@yzyinc.com 877-999-3534
Tottenham, London N17 OQT, UK
MADE IN USA

Total White Brightening Body Lotion diminshes dark spots and skin discolorations caused by acne, aging, sun damage, and pregnancy. This special formula is fortified with Carrot Oil and Vitamins A and E to help restore and maintain skin's essentialmoisture balance leaving your skin feeling beautifully softand smooth. This light, fast absorbing lotion safely fades and evens complexion for younger and healthier looking skin.